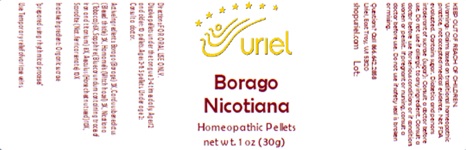 DRUG LABEL: Borago Nicotiana
NDC: 48951-2078 | Form: PELLET
Manufacturer: Uriel Pharmacy Inc.
Category: homeopathic | Type: HUMAN OTC DRUG LABEL
Date: 20240917

ACTIVE INGREDIENTS: BORAGO OFFICINALIS WHOLE 3 [hp_X]/1 1; CENTAUREA BENEDICTA 3 [hp_X]/1 1; HAMAMELIS VIRGINIANA LEAF 3 [hp_X]/1 1; TOBACCO LEAF 6 [hp_X]/1 1; ALUMINUM OXIDE 8 [hp_X]/1 1; HORSE CHESTNUT 10 [hp_X]/1 1; FERROUS ARSENATE 10 [hp_X]/1 1
INACTIVE INGREDIENTS: SUCROSE

Borago Nicotiana

INDICATIONS AND USAGE

Directions: FOR ORAL USE ONLY.

DOSAGE AND ADMINISTRATION

Dissolve pellets under the tongue 3-4 times daily. Ages 12 and older: 10 pellets. Ages 2-11: 5 pellets. Under age 2: Consult a doctor.

Active Ingredients: Borago (Borage) 3X,
Carduus benedictus (Blessed thistle) 3X,
Hamamelis (Witch hazel) 3X, Nicotiana (Tobacco)
6X, Sapphire (Blue corundum containing traces of iron and titanium) 8X, Aesculus (Horse chestnut seed) 10X, Scorodite (Nat. ferric arsenate) 10X

Inactive Ingredient: Organic sucrose

Prepared using rhythmical processes.

PURPOSE

Use: Temporary relief of varicose veins.

KEEP OUT OF REACH OF CHILDREN.

WARNINGS

Warnings: Claims based on traditional homeopathic practice, not accepted medical evidence. Not FDA evaluated. Contains sugar. Diabetics and persons intolerant of sucrose (sugar): Consult a doctor before use. Do not use if allergic to any ingredient. Consult a doctor before use for serious conditions or if conditions worsen or persist. If pregnant or nursing, consult a doctor before use. Do not use if safety seal is broken or missing.

QUESTIONS

Questions? Call 866.642.2858 Uriel, East Troy, WI 53120 shopuriel.com